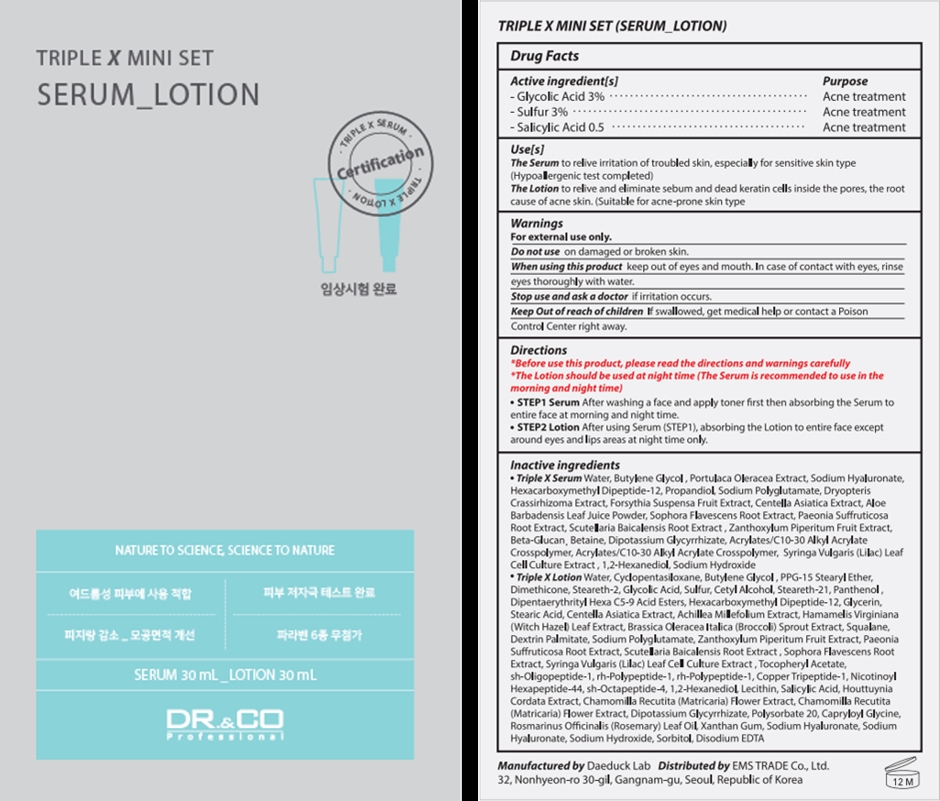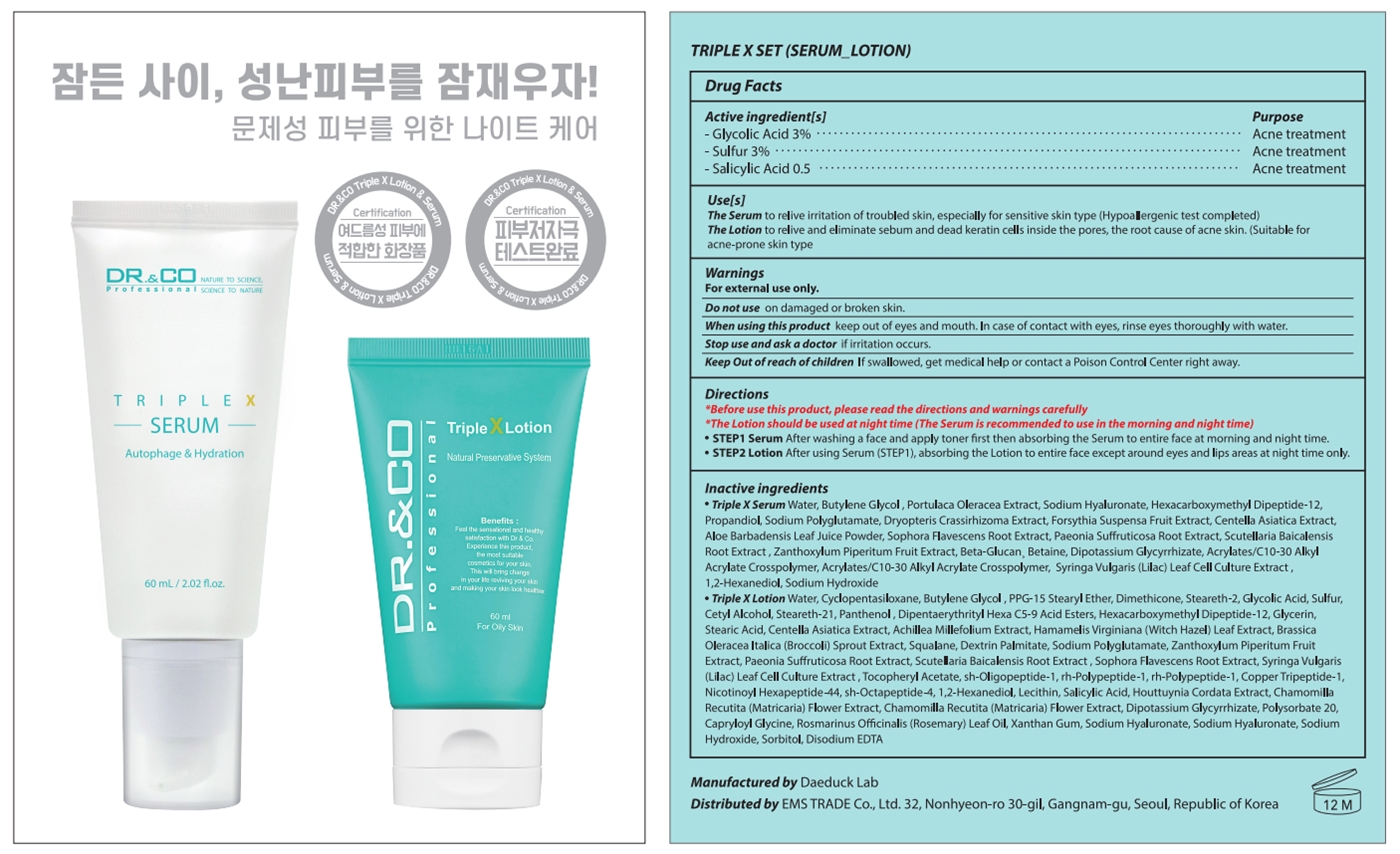 DRUG LABEL: Triple X-Lotion
NDC: 80724-201 | Form: LOTION
Manufacturer: EMS TRADE
Category: otc | Type: HUMAN OTC DRUG LABEL
Date: 20231212

ACTIVE INGREDIENTS: SALICYLIC ACID 0.5 g/100 mL; GLYCOLIC ACID 3 g/100 mL; SULFUR 3 g/100 mL
INACTIVE INGREDIENTS: SCUTELLARIA BAICALENSIS ROOT; .ALPHA.-TOCOPHEROL ACETATE; CAPRYLOYL GLYCINE; CYCLOMETHICONE 5; DIPENTAERYTHRITYL HEXA C5-9 ACID ESTERS; BROCCOLI SPROUT; PANTHENOL; NEPIDERMIN; BASIC FIBROBLAST GROWTH FACTOR (HUMAN); LECITHIN, SOYBEAN; CHAMOMILE; STEARETH-2; SOPHORA FLAVESCENS ROOT; PREZATIDE COPPER; 1,2-HEXANEDIOL; BUTYLENE GLYCOL; PPG-15 STEARYL ETHER; STEARETH-21; GLYCERIN; STEARIC ACID; SODIUM HYDROXIDE; ZANTHOXYLUM PIPERITUM FRUIT PULP; PAEONIA SUFFRUTICOSA ROOT; SQUALANE; DEXTRIN PALMITATE (CORN; 20000 MW); HYALURONATE SODIUM; POLYSORBATE 20; CENTELLA ASIATICA WHOLE; ACHILLEA MILLEFOLIUM WHOLE; HAMAMELIS VIRGINIANA LEAF; CETYL ALCOHOL; ROSEMARY OIL; WATER; DIMETHICONE; HOUTTUYNIA CORDATA FLOWERING TOP; GLYCYRRHIZINATE DIPOTASSIUM; XANTHAN GUM; SORBITOL; EDETATE DISODIUM ANHYDROUS

80724-201

Active ingredient[s]

Glycolic Acid 3%

Sulfur 3%

Salicylic Acid 0.5%

Purpose

Acne treatment

Use[s]

The Serum to relive irritation of troubled skin, especially for sensitive skin type (Hypoallergenic test completed)

The Lotion to relive and eliminate sebum and dead keratin cells inside the pores, the root cause of acne skin. (Suitable for acne-prone skin type)

Warnings

For external use only.

Do not use on damaged or broken skin.

When using this product keep out of eyes and mouth. In case of contact with eyes, rinse eyes thoroughly with water.

Stop use and ask a doctor

if irritation occurs.

Keep out of reach of children

If swallowed, get medical help or contact a Poison Control Center right away.

Directions

*Before use this product, please read the directions and warnings carefully

*The Lotion should be used at night time (The Serum is recommended to use in the morning and night time)

- STEP1 Serum After washing a face and apply toner first then absorbing the Serum to entire face at morning and night time.
- STEP2 Lotion After using Serum (STEP1), absorbing the Lotion to entire face except around eyes and lips areas at night time only.

Inactive ingredients

- Triple X Serum Water, Butylene Glycol , Portulaca Oleracea Extract, Sodium Hyaluronate, Hexacarboxymethyl Dipeptide-12, Propandiol, Sodium Polyglutamate, Dryopteris Crassirhizoma Extract, Forsythia Suspensa Fruit Extract, Centella Asiatica Extract, Aloe Barbadensis Leaf Juice Powder, Sophora Flavescens Root Extract, Paeonia Suffruticosa Root Extract, Scutellaria Baicalensis Root Extract , Zanthoxylum Piperitum Fruit Extract, Beta-Glucan¸ Betaine, Dipotassium Glycyrrhizate, Acrylates/C10-30 Alkyl Acrylate Crosspolymer, Acrylates/C10-30 Alkyl Acrylate Crosspolymer, Syringa Vulgaris (Lilac) Leaf Cell Culture Extract , 1,2-Hexanediol, Sodium Hydroxide
- Triple X Lotion Water, Cyclopentasiloxane, Butylene Glycol , PPG-15 Stearyl Ether, Dimethicone, Steareth-2, Cetyl Alcohol, Steareth-21, Panthenol , Dipentaerythrityl Hexa C5-9 Acid Esters, Hexacarboxymethyl Dipeptide-12, Glycerin, Stearic Acid, Centella Asiatica Extract, Achillea Millefolium Extract, Hamamelis Virginiana (Witch Hazel) Leaf Extract, Brassica Oleracea Italica (Broccoli) Sprout Extract, Squalane, Dextrin Palmitate, Sodium Polyglutamate, Zanthoxylum Piperitum Fruit Extract, Paeonia Suffruticosa Root Extract, Scutellaria Baicalensis Root Extract , Sophora Flavescens Root Extract, Syringa Vulgaris (Lilac) Leaf Cell Culture Extract , Tocopheryl Acetate, sh-Oligopeptide-1, rh-Polypeptide-1, rh-Polypeptide-1, Copper Tripeptide-1, Nicotinoyl Hexapeptide-44, sh-Octapeptide-4, 1,2-Hexanediol, Lecithin, Houttuynia Cordata Extract, Chamomilla Recutita (Matricaria) Flower Extract, Chamomilla Recutita (Matricaria) Flower Extract, Dipotassium Glycyrrhizate, Polysorbate 20, Capryloyl Glycine, Rosmarinus Officinalis (Rosemary) Leaf Oil, Xanthan Gum, Sodium Hyaluronate, Sodium Hyaluronate, Sodium Hydroxide, Sorbitol, Disodium EDTA